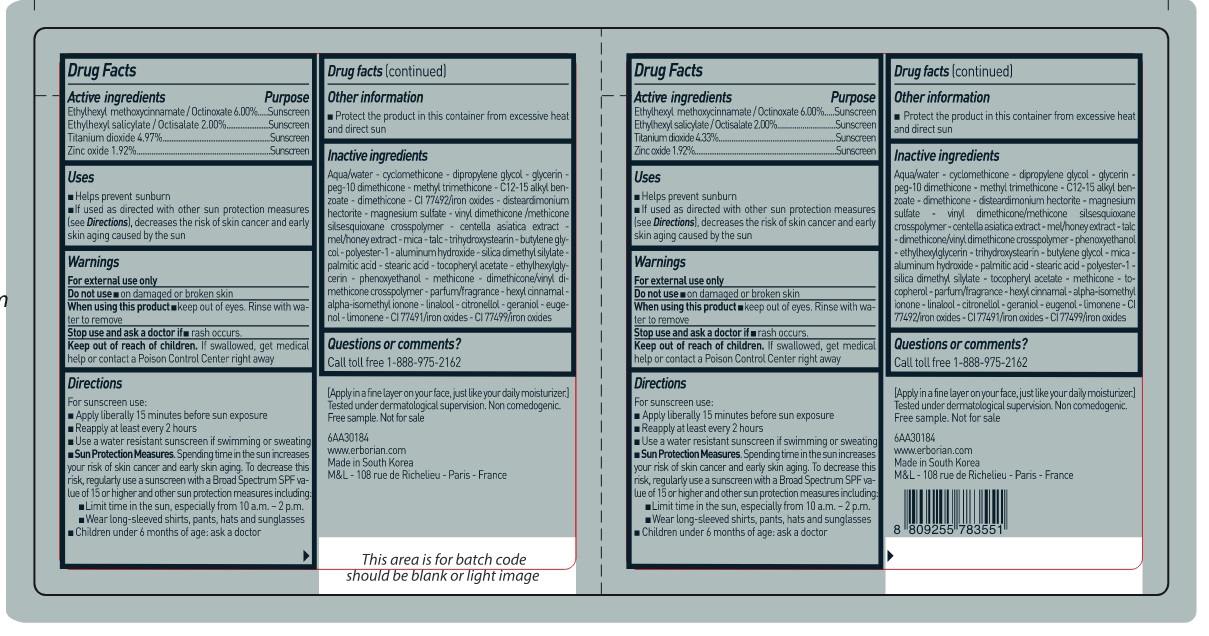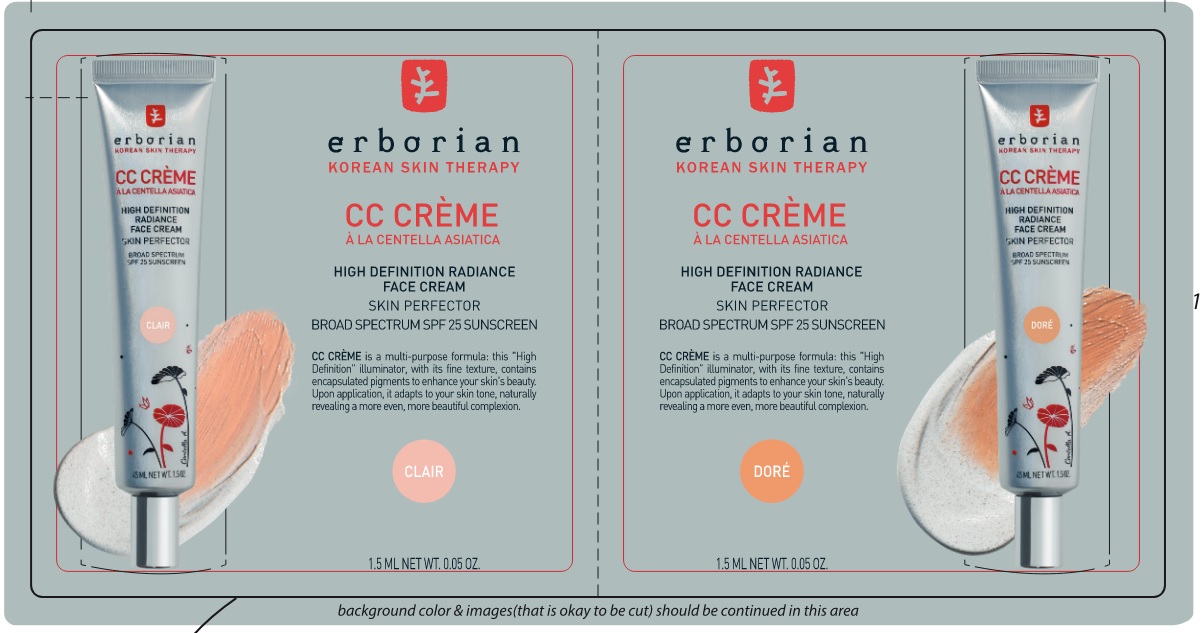 DRUG LABEL: ERBORIAN DOUBLE SAMPLE CC CREME CLAIR and DORE SPF 25
NDC: 10345-921 | Form: KIT | Route: TOPICAL
Manufacturer: LABORATOIRES M&L
Category: otc | Type: HUMAN OTC DRUG LABEL
Date: 20250109

ACTIVE INGREDIENTS: OCTINOXATE 60 mg/1 mL; OCTISALATE 20 mg/1 mL; TITANIUM DIOXIDE 43.3 mg/1 mL; ZINC OXIDE 19.2 mg/1 mL; OCTISALATE 20 mg/1 mL; OCTINOXATE 60 mg/1 mL; TITANIUM DIOXIDE 49.7 mg/1 mL; ZINC OXIDE 19.2 mg/1 mL
INACTIVE INGREDIENTS: MAGNESIUM SULFATE, UNSPECIFIED FORM; CENTELLA ASIATICA; HONEY; MICA; ALUMINUM HYDROXIDE; PALMITIC ACID; STEARIC ACID; SILICA DIMETHYL SILYLATE; .ALPHA.-TOCOPHEROL ACETATE; METHICONE (20 CST); TOCOPHEROL; .ALPHA.-HEXYLCINNAMALDEHYDE; ISOMETHYL-.ALPHA.-IONONE; LINALOOL, (+/-)-; WATER; CYCLOMETHICONE; DIPROPYLENE GLYCOL; GLYCERIN; METHYL TRIMETHICONE; ALKYL (C12-15) BENZOATE; DIMETHICONE; DISTEARDIMONIUM HECTORITE; .BETA.-CITRONELLOL, (R)-; GERANIOL; EUGENOL; LIMONENE, (+)-; FERRIC OXIDE YELLOW; FERRIC OXIDE RED; FERROSOFERRIC OXIDE; WATER; CYCLOMETHICONE; DIPROPYLENE GLYCOL; GLYCERIN; METHYL TRIMETHICONE; ALKYL (C12-15) BENZOATE; DIMETHICONE; DISTEARDIMONIUM HECTORITE; MAGNESIUM SULFATE, UNSPECIFIED FORM; CENTELLA ASIATICA; HONEY; MICA; TALC; TRIHYDROXYSTEARIN; BUTYLENE GLYCOL; ALUMINUM HYDROXIDE; PALMITIC ACID; STEARIC ACID; SILICA DIMETHYL SILYLATE; .ALPHA.-TOCOPHEROL ACETATE; ETHYLHEXYLGLYCERIN; PHENOXYETHANOL; METHICONE (20 CST); .ALPHA.-HEXYLCINNAMALDEHYDE; ISOMETHYL-.ALPHA.-IONONE; LINALOOL, (+/-)-; .BETA.-CITRONELLOL, (R)-; GERANIOL; EUGENOL; LIMONENE, (+)-; FERRIC OXIDE YELLOW; FERROSOFERRIC OXIDE

ERBORIAN - DOUBLE SAMPLE CC CREME CLAIR & DORE SPF 25

Active ingredients

Ethylhexyl methoxycinnamate / Octinoxate 6.00%

Ethylhexyl salicylate / Octisalate 2.00%

Titanium dioxide 4.97%

Zinc oxide 1.92%

Purpose

Sunscreen

Uses

- Helps prevent sunburn
- If used as directed with other sun protection measures (see Directions), decreases the risk of skin cancer and early skin aging caused by the sun

Warnings

For external use only

Do not use

- on damaged or broken skin

When using this product

keep out of eyes. Rinse with water to remove

Stop use and ask a doctor if

1. rash occurs.

Keep out of reach of children.

If swallowed, get medical help or contact a Poison Control Center right away

Directions

For sunscreen use:

- Apply liberally 15 minutes before sun exposure
- Reapply at least every 2 hours
- Use a water resistant sunscreen if swimming or sweating
- SunProtectionMeasures. Spending time in the sun increases your riskofskincancerandearlyskinaging. Todecreasethisrisk, regularly use a sunscreen with a Broad Spectrum SPF value of 15 or higher and other sun protection measures including:
- Limit time in the sun, especially from 10 a.m. –2 p.m.
- Wear long-sleeved shirts, pants, hats and sunglasses
- Children under 6 months of age: Ask a doctor

Other information

- Protect the product in this container from excessive heat and direct sun

Inactive ingredients

Aqua/water - cyclomethicone - dipropylene glycol - glycerin - peg-10 dimethicone - methyl trimethicone - C12-15 alkyl benzoate - dimethicone - CI 77492/iron oxides - disteardimonium hectorite - magnesium sulfate - vinyl dimethicone /methicone silsesquioxane crosspolymer - centella asiatica extract - mel/honey extract - mica - talc - trihydroxystearin - butylene glycol - polyester-1 - aluminum hydroxide - silica dimethyl silylate - palmitic acid - stearic acid - tocopheryl acetate - ethylhexylglycerin - phenoxyethanol - methicone - dimethicone/vinyl imethicone crosspolymer - parfum/fragrance - hexyl cinnamal - alpha-isomethyl ionone - linalool - citronellol - geraniol - eugenol - limonene - CI 77491/iron oxides - CI 77499/iron oxides

Questions or comments?

Call toll free 1-888-975-2162

Active ingredients

Ethylhexyl methoxycinnamate / Octinoxte 6.00%

Ethylhexyl salicylate / Octisalate 2.00%

Titanium Dioxide 4.33%

Zinc oxide 1.92%

Purpose

Sunscreen

Uses

- Helps prevent sunburn
- if used as directed with other sun protection measures [ see Directions], decreases the risk of skin cancer andearly skin aging caused by the sun

Warnings

For external use only

Do not use

- on damaged or broken skin

When using this product

- keep out of eyes. Rinse with water to remove

Stop use and ask a doctor if

- rash occurs

Keep out of reach of children.

If swallowed, get medical help or contact a Poison Control Center right away.

Directions

For sunscreen use:

- Apply liberally 15 minutes before sun exposure.
- Reapply at least every 2 hours
- Use a water resistant sunscreen if swimming or sweating
- Sun Protection Meausres. Spending time in the sun incerases your risk of skin cancer and early skin aging. To decrease this risk, regularly use a sunscreen with a Broad Spectrum SPF value of 15 or higher and other sun protection measures including:
- Limit time in the sun, especially from 10 a.m. - 2 p.m.
- Wear long-sleeved shirts, pants, hats and sunglasses
- Children under 6 months of age: Ask a doctor.

Other information

- Protect the product in this container from excessive heat and direct sun

Inactive ingredients

qua/water - cyclomethicone - dipropylene glycol - glycerin - peg-10 dimethicone - methyl trimethicone - C12-15 alkyl benzoate - dimethicone - disteardimonium hectorite - magnesium sulfate - vinyl dimethicone/methicone silsesquiocane crosspolymer - centella asiatica extract - mel/honey extract - talc - dimethicone/vinyl dimethicone crosspolymer - phenoxyethanol - ethylhexylglycerin - trihydroxystearn - butylene glycol - mica - aluminum hydroxide - palmitic acid - stearicacid - polyester-1 - silica dimethyl silyate - tocopheryl acetate - methicone - tocopherol - parfum/fragrance - hexyl cinnamal - alpha-isomethyl ionone - linalool - citronellol - geraniol - eugenol - limonene - CI 77492/iron oxides - CI 77491/Iron oxides - CI77499/iron oxides

Questions or comments?

Call toll free 1-888-975-2162